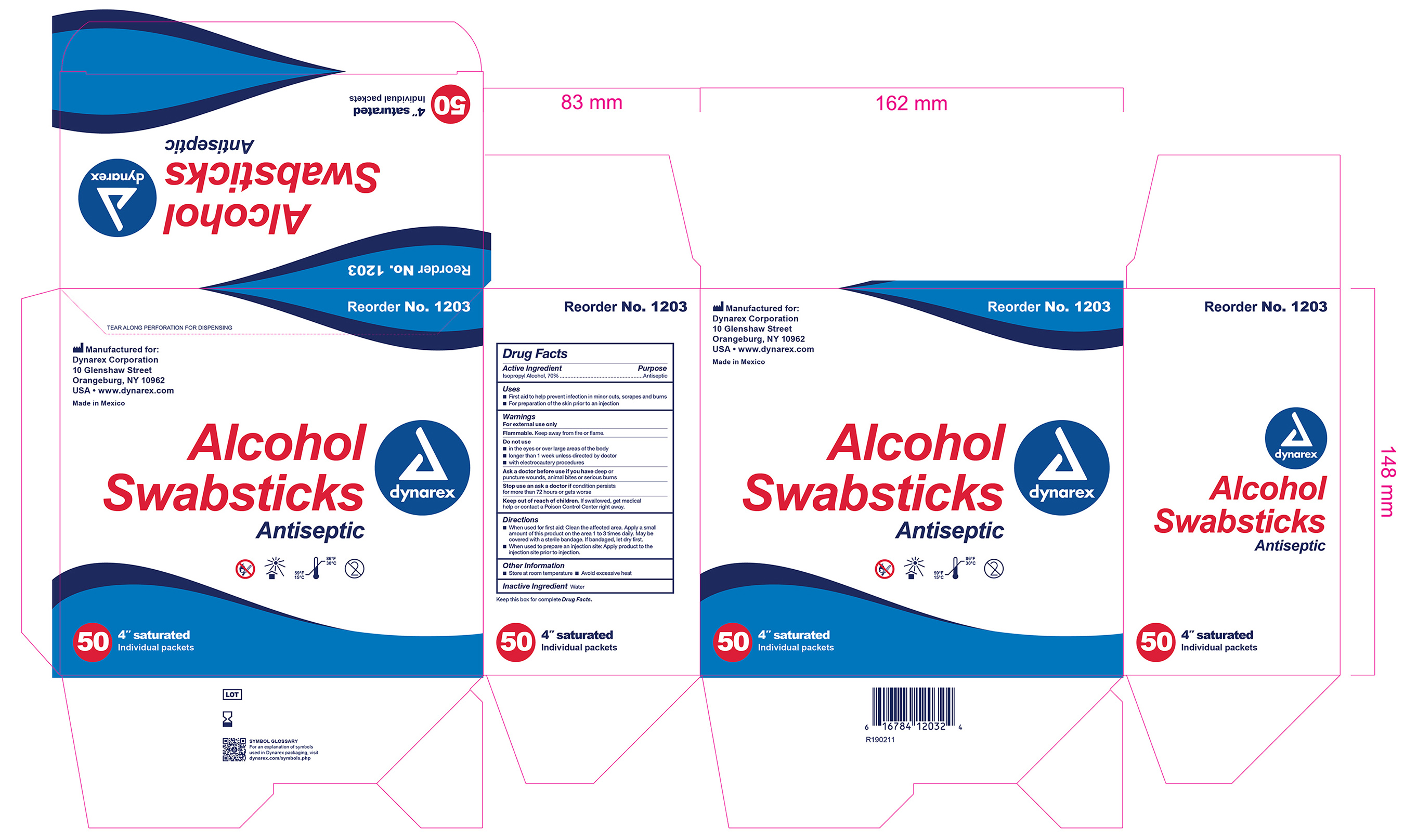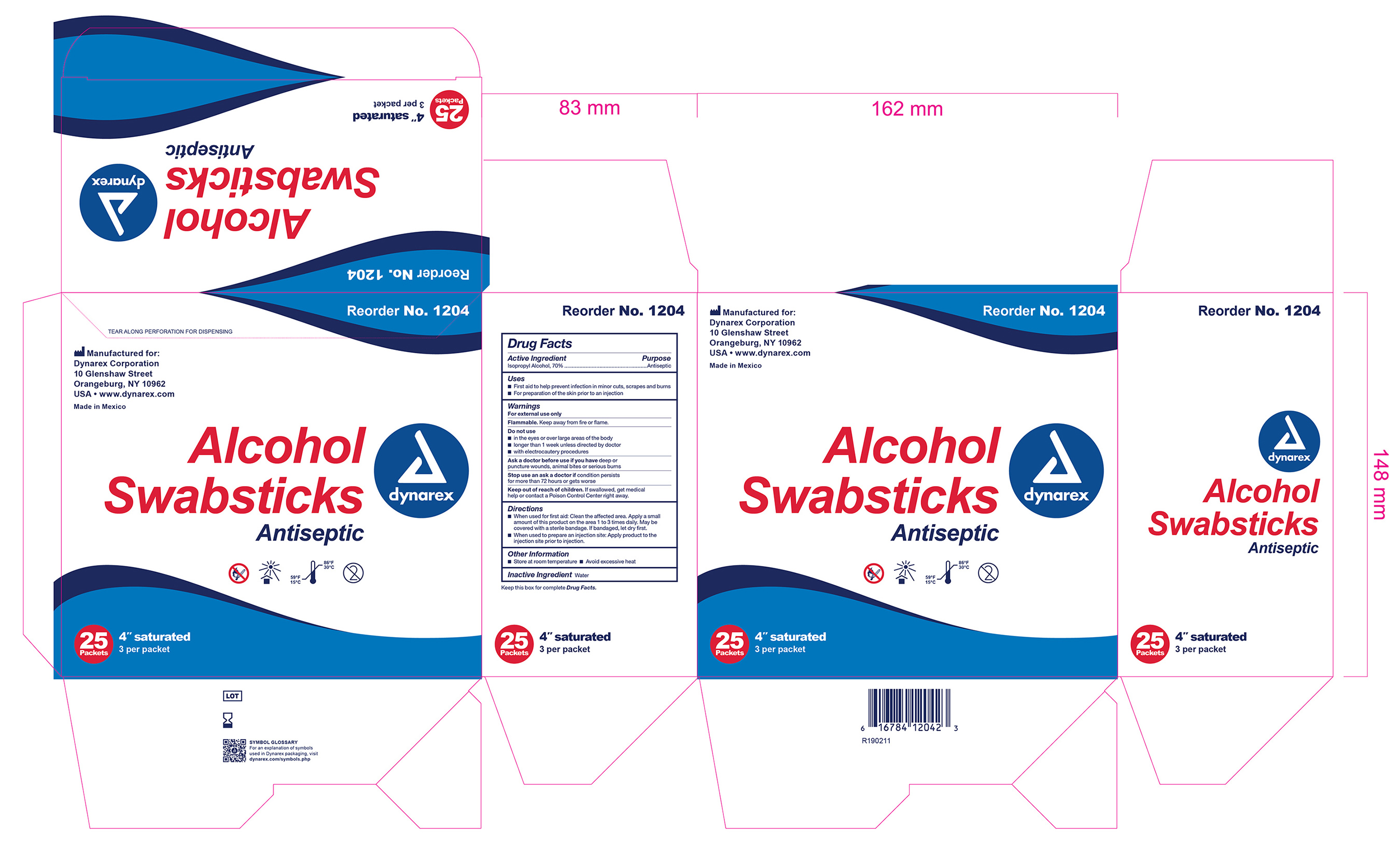 DRUG LABEL: Alcohol
NDC: 67777-300 | Form: SWAB
Manufacturer: Dynarex Corporation
Category: otc | Type: HUMAN OTC DRUG LABEL
Date: 20251218

ACTIVE INGREDIENTS: ISOPROPYL ALCOHOL 0.7 mL/1 mL
INACTIVE INGREDIENTS: WATER

1203 Alcohol Swabsticks NDC 67777-300-01
1204 Alcohol Swabsticks NDC 67777-300-02

Active Ingredient Purpose

Isopropyl Alcohol 70% v/v Antiseptic

Use:

For preparation of the skin prior to injection.

Warnings:

- For external use only
- Flammable, keep away from flame or fire
- Not for use with electrocautinary devices or procedures
- Do not use in eyes

Indications and Usage:

Stop use and ask a doctor if:

- Irritation or redness develops
- condition persists for more than 72 hours
- Cleansing of an injection site

Keep out of reach of children.

In case of accidental ingestion, seek professional assistance or consult a poison control center immediately.

Directions:

Wipe injection site vigorously and discard

Other information:

- Store at room temperature: 15 deg C to 30 deg C 59 deg F to 86 deg F
- avoid excessive heat

Inactive Ingredient

- Water

Principal Display Panel

1203 Alcohol Swabstick 67777-300-01

1204 Alcohol Swabstick 67777-300-02